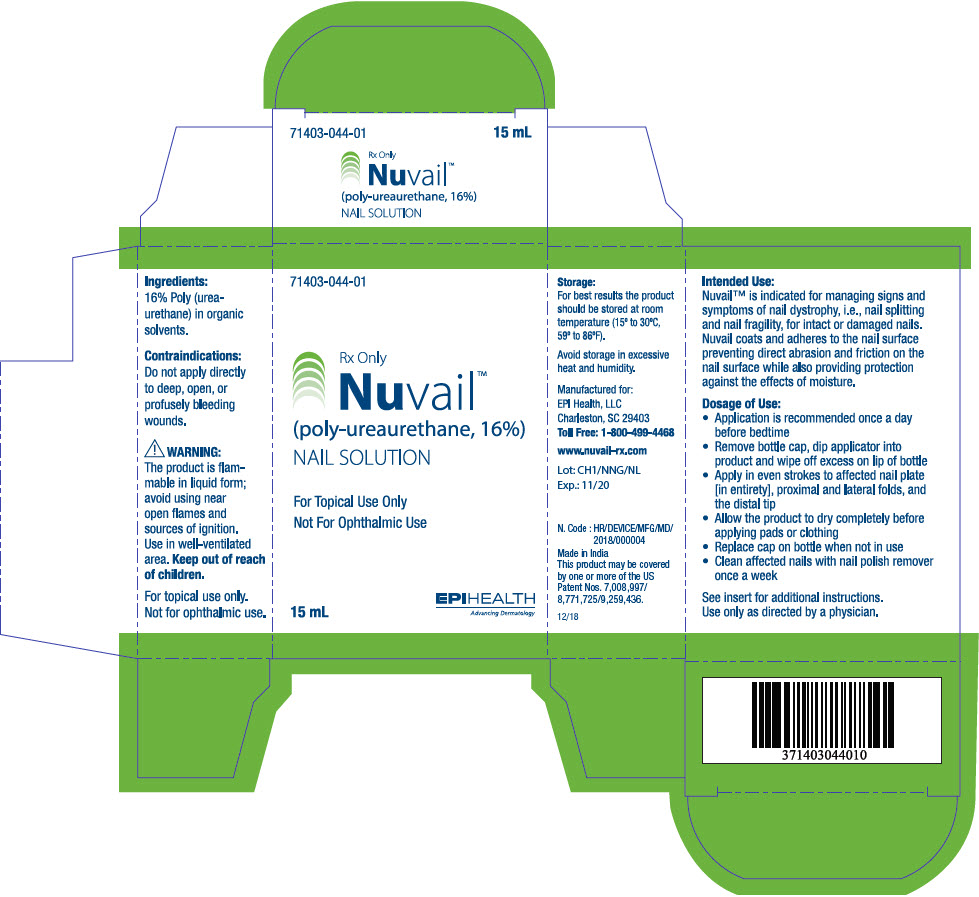 DRUG LABEL: Nuvail
NDC: 71403-044 | Form: LIQUID
Manufacturer: EPI Health, Inc
Category: other | Type: PRESCRIPTION MEDICAL DEVICE LABEL
Date: 20190117

ACTIVE INGREDIENTS: LAURIC ACID 2.4 mg/15 mL

Nuvail™
(poly-ureaurethane, 16%)

NAIL SOLUTION

Rx Only

INTENDED USE

Nuvail™ is indicated for managing signs and symptoms of nail dystrophy, i.e., nail splitting and nail fragility, for intact or damaged nails. Nuvail coats and adheres to the nail surface preventing direct abrasion and friction on the nail surface while also providing protection against the effects of moisture.

PRODUCT DESCRIPTION

The product is a biocompatible, polymeric solution which forms a uniform film when applied to the nail. The product is dispersed in a non-cytotoxic solution which dries rapidly, adhering to the contours of the nail to form a flexible, waterproof barrier. The film will wear off naturally and must be re-applied as directed to be effective. The film is colorless, transparent and possesses good moisture vapor permeability.

INGREDIENTS

16% Poly (urea-urethane) in organic solvents.

CONTRAINDICATIONS

Do not apply directly to deep, open, or profusely bleeding wounds.

WARNINGS AND PRECAUTIONS

PRECAUTIONS

The product is flammable in liquid form; avoid using near open flames and sources of ignition. Use in well-ventilated area. Keep out of reach of children.

Store at room temperature away from heat. Do not allow product to come into contact with floors, counter tops, furniture or other finished surfaces - will stain.

May temporarily sting upon application. Persons sensitized to isocyanate should not use this product. Should redness or other signs of irritation appear, discontinue use and consult your healthcare provider.

Use of other products, ointments, creams or lotions before application of this product may prevent the film from forming correctly and reduce effectiveness.

DIRECTIONS FOR USE

- Application is recommended once a day before bedtime
- Remove bottle cap, dip applicator into product and wipe off excess on lip of bottle
- Apply in even strokes to affected nail plate [in entirety], proximal and lateral folds, and the distal tip
- Allow the product to dry completely before applying pads or clothing
- Replace cap with applicator on bottle when not in use
- Clean affected nails with nail polish remover once a week

HOW SUPPLIED

Nuvail Nail Solution is supplied in a:

15 ml non-sterile bottle with applicator 71403-044-01.

STORAGE AND SHELF LIFE

For best results the product should be stored at room temperature (15° to 30°C, 59° to 86°F).

Avoid storage in excessive heat and humidity. Refer to the bottle label for expiration date.

Manufactured for:
EPI Health, LLC
Charleston, SC 29403
Toll Free: 1-800-499-4468

www.nuvail-rx.com

N. Code : HR/DEVICE/MFG/MD/2018/000004
Made in India

December 2018

This product may be covered by one or more of the US Patent Nos. 7,008,997/8,771,725/9,259,436.

NUV-PI-0617

Version - 1

PRINCIPAL DISPLAY PANEL - 15 mL Bottle Carton

71403-044-01

Rx Only
Nuvail™
(poly-ureaurethane, 16%)
NAIL SOLUTION

For Topical Use Only
Not For Ophthalmic Use

EPIHEALTH
Advancing Dermatology

15 mL